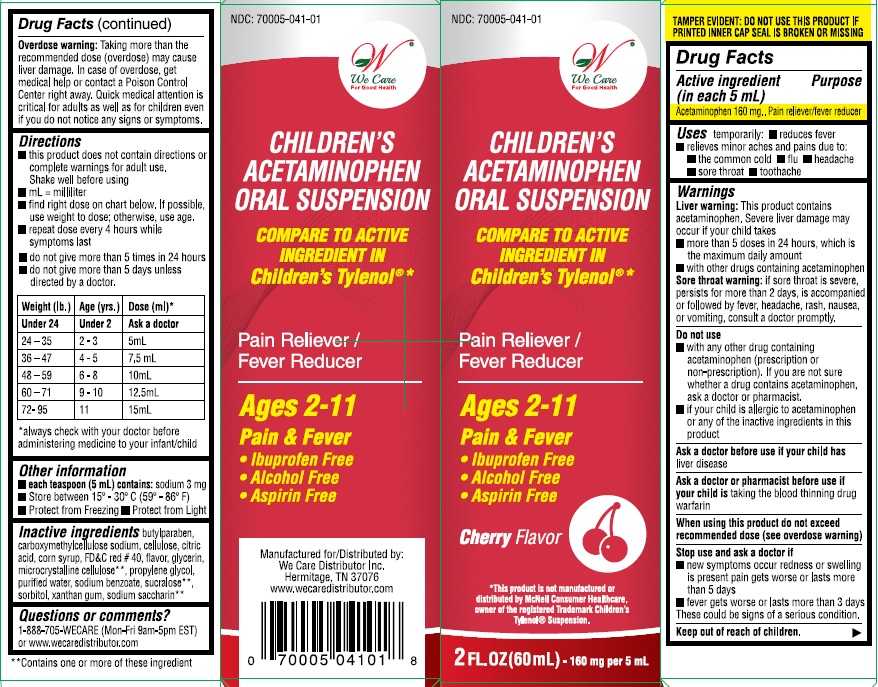 DRUG LABEL: Childrens Acetaminophen
NDC: 70005-041 | Form: SUSPENSION
Manufacturer: We Care Distributors Inc.
Category: otc | Type: HUMAN OTC DRUG LABEL
Date: 20160817

ACTIVE INGREDIENTS: Acetaminophen 160 mg/5 mL
INACTIVE INGREDIENTS: BUTYLPARABEN; CARBOXYMETHYLCELLULOSE SODIUM; CELLULOSE, MICROCRYSTALLINE; CITRIC ACID MONOHYDRATE; GLYCERIN; HIGH FRUCTOSE CORN SYRUP; PROPYLENE GLYCOL; WATER; FD&C Red No. 40; SODIUM BENZOATE; SACCHARIN SODIUM; SUCRALOSE; SORBITOL; XANTHAN GUM

Drug Facts

Active Ingredient (in each 5 mL)

Acetaminophen 160 mg

Purpose

Acetaminophen.............................Pain reliever/fever reducer

Uses

- temporarily reduces fever
- temporarily relieves minor aches and pains due to:
- the common cold
- flu
- headache
- sore throat
- toothache

Warnings

Liver warning: This product contains acetaminophen. Severe liver damage may occur if your child takes:
• more than 5 doses in 24 hours, which is the maximum daily amount
• with other drugs containing acetaminophen
Sore throat warning: If sore throat is severe, persists for more than 2 days, is accompanied or followed by fever, headache, rash, nausea, or vomiting, consult a doctor promptly.

Do not use

- with any other drug containing acetaminophen (prescription or non-prescription). If you are not sure whether a drug contains acetaminophen, ask a doctor or pharmacist.
- if your child is allergic to acetaminophen or any of the inactive ingredients in this this product.

Ask a doctor before use if your child has

liver disease.

Ask a doctor or pharmacist before use if your child is

taking the blood thinning drug warfarin.

When using this product

• do not exceed recommended dose (see overdose warning)

Stop use and ask a doctor if

• new symptoms occur
• redness or swelling is present
• pain gets worse or lasts more than 5 days
• fever gets worse or lasts more than 3 days
These could be signs of a serious condition.

Keep out of the reach of children.

Overdose Warning: Taking more than the recommended dose (overdose) may cause liver damage. In case of accidental overdose, seek
professional assistance or contact a Poison Control Center immediately. Quick medical attention is critical even if you do not notice any signs or
symptoms.

Directions

• this product does not contain directions or complete warnings for adult use.
• shake well before using

• mL = milliliter
• find right dose on chart below. If possible, use weight to dose; otherwise, use age.
• use only enclosed dosing cup designed for use with this product. Do not use any other dosing device.
• repeat dose every 4 hours while symptoms last
• do not give more than 5 times in 24 hours
• do not give more than 5 days unless directed by a doctor
Weight (lb.) Age (yrs.) Dose (mL*)
under 24 under 2 ask a doctor
24-35 2-3 5 mL
36-47 4-5 7.5 mL
48-59 6-8 10 mL
60-71 9-10 12.5 mL
72-95 11 15 mL

* always check with your doctor before administering medicine to your infant/child

Other information

- each teaspoon (mL) contains: Sodium 3 mg
- store between 15^0-30^0C (59^0-86^0F)
- Protect from freezing
- Protect from light

Inactive Ingredients

butylparaben, carboxymethylcellulose sodium, cellulose, citric acid, corn syrup, FD&C red #40, flavor, glycerin, microcrystalline cellulose, propylene glycol, purified water, sodium benzoate, sodium saccharin, sorbitol, sucralose, xanthan gum

Questions or Comments?

1-888-705-WECARE (Mon-Fri 9am-5pm EST) or www.wecaredistributor.com

Principal Display Panel

Compare to the active ingredient in Children's Tylenol®*
Children's Pain Relief
Suspension Liquid
Cherry Flavor
For ages 2 to 11
2 FL OZ (60 mL)